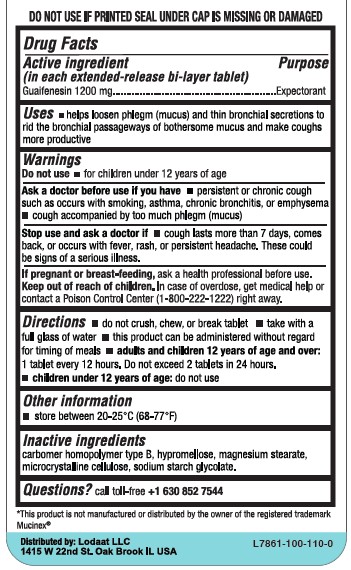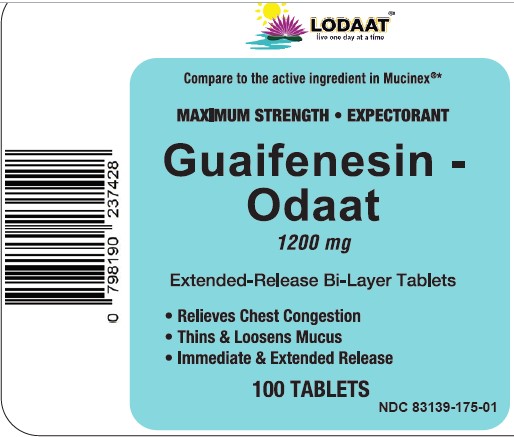 DRUG LABEL: GUAIFENESIN - ODAAT
NDC: 83139-175 | Form: TABLET
Manufacturer: LODAAT LLC
Category: otc | Type: HUMAN OTC DRUG LABEL
Date: 20230304

ACTIVE INGREDIENTS: GUAIFENESIN 1200 mg/1 1
INACTIVE INGREDIENTS: CARBOMER HOMOPOLYMER TYPE B (ALLYL PENTAERYTHRITOL CROSSLINKED); MAGNESIUM STEARATE; MICROCRYSTALLINE CELLULOSE; SODIUM STARCH GLYCOLATE TYPE A; HYPROMELLOSE, UNSPECIFIED

LODAAT- GUAIFENESIN - ODAAT 1200 mg CAPLETS (83139-175)

ACTIVE INGREDIENT (IN EACH EXTENDED-RELEASE BI-LAYER TABLET)

GUAIFENESIN 1200MG

PURPOSE

EXPECTORANT

USES

- HELPS LOOSEN PHLEGM (MUCUS) AND THIN BRONCHIAL SECRETIONS TO RID THE BRONCHIAL PASSAGEWAY OF BOTHERSOME MUCUS AND MAKE COUGHS MORE PRODUCTIVE

WARNINGS

DO NOT USE

- FOR CHILDREN UNDER 12 YEARS OF AGE

ASK DOCTOR BEFORE USE IF YOU HAVE:

- PERSISTENT OR CHRONIC COUGH SUCH AS OCCURS WITH SMOKING, ASTHMA, CHRONIC BRONCHITIS OR EMPHASEMA (MUCUS)
- COUGH ACCOMPANIED BY EXCESSIVE PHLEGM

STOP USE AND ASK A DOCTOR IS

- COUGH LASTS FOR MORE THAN 7 DAYS, RECURS, OR IS ACCOMPANIED BY FEVER, RASH, OR PERSISTENT HEADACHE. THESE COULD BE SIGNS OF A SERIOUS CONDITION.

IF PREGNANT OR BREAST FEEDING, ASK A HEALTH PROFESSIONAL BEFORE USE.

KEEP OUT OF REACH OF CHILDREN. IN CASE OF OVERDOSE, GET MEDICAL HELP OR CONTACT A POISON CONTROL CENTER (1-800-222-1222) IMMEDIATELY.

DIRECTIONS

- DO NOT CRUSH, CHEW, OR BREAK TABLET
- TAKE WITH A FULL GLASS OF WATER
- THIS PRODUCT CAN BE ADMINISTERED WITHOUT REGARD FOR TIMING OF MEALS
- ADULTS AND CHILDREN 12 YEARS OF AGE AND OVER: TAKE 1 TABLET EVERY 12 HOURS. DO NOT EXCEED 2 TABLETS IN 24 HOURS.
- CHILDREN UNDER 12 YEARS OF AGE: DO NOT USE.

OTHER INFORMATION

- STORE BETWEEN 20-25°C (68-77°F)

INACTIVE INGREDIENTS

CARBOMER HOMOPOLYMER TYBE B, HYPROMELLOSE, MAGNESIUM STEARATE, MICROCRYSTALLINE CELLULOSE, SODIUM STARCH GLYCOLATE.

QUESTIONS?

CALL TOLL-FREE +1 630 852 7544